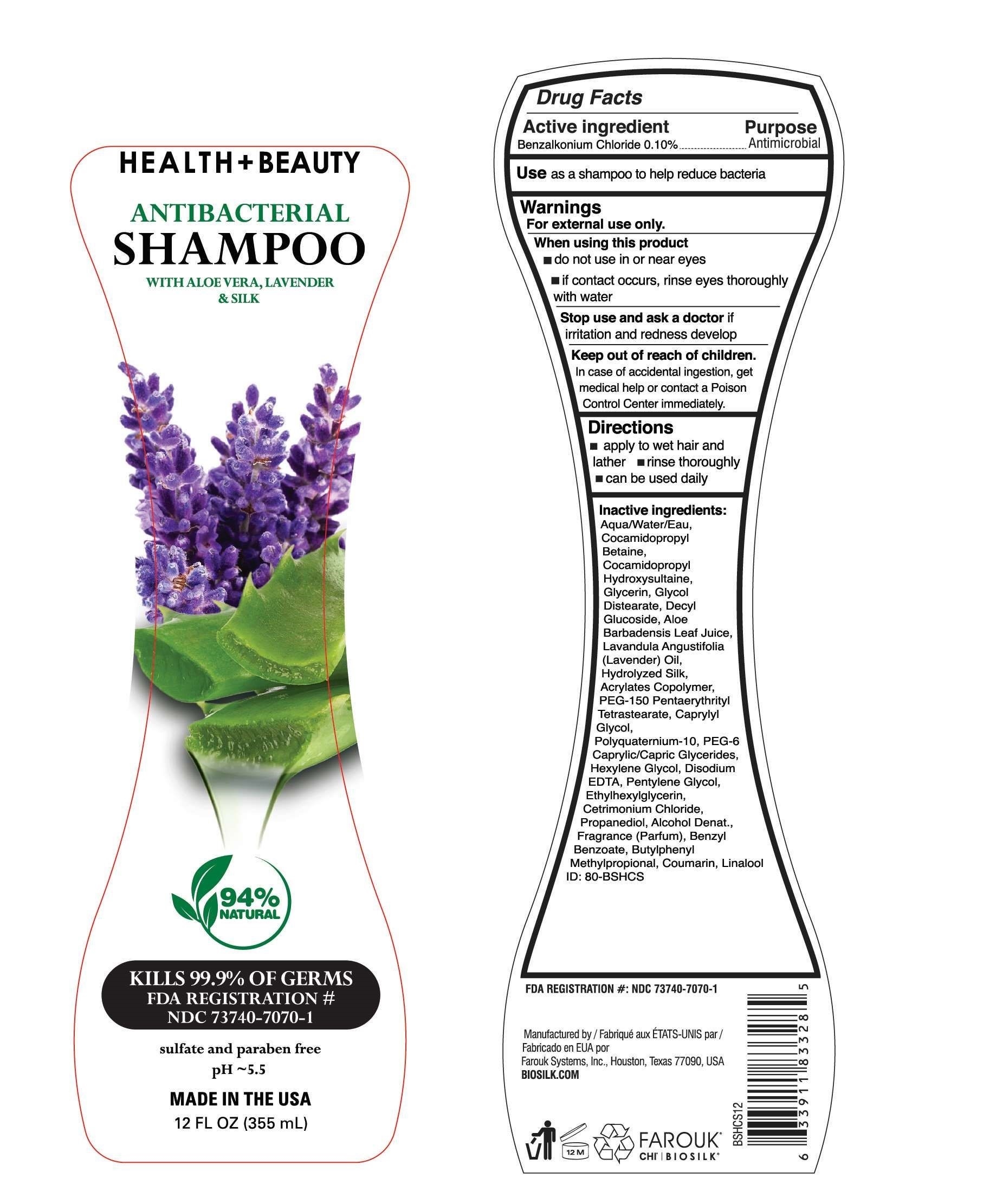 DRUG LABEL: Biosilk
NDC: 73740-7070 | Form: SHAMPOO
Manufacturer: Farouk Systems, Inc.
Category: otc | Type: HUMAN OTC DRUG LABEL
Date: 20200930

ACTIVE INGREDIENTS: BENZALKONIUM CHLORIDE 0.1 g/100 g
INACTIVE INGREDIENTS: PEG-150 PENTAERYTHRITYL TETRASTEARATE 0.528 g/100 g; POLYQUATERNIUM-10 (1000 MPA.S AT 2%) 0.27 g/100 g; PEG-6 CAPRYLIC/CAPRIC GLYCERIDES 0.264 g/100 g; HEXYLENE GLYCOL 0.2 g/100 g; FRAGRANCE LAVENDER & CHIA F-153480 0.355 g/100 g; COCAMIDOPROPYL HYDROXYSULTAINE 4 g/100 g; CAPRYLYL GLYCOL 0.5 g/100 g; WATER 70.647 g/100 g; ETHYLHEXYLGLYCERIN 0.1 g/100 g; PENTYLENE GLYCOL 0.15 g/100 g; ALCOHOL 0.014 g/100 g; EDETIC ACID 0.15 g/100 g; BENZYL BENZOATE 0.5 g/100 g; DECYL GLUCOSIDE 1.5 g/100 g; BUTYL ACRYLATE/METHYL METHACRYLATE/METHACRYLIC ACID COPOLYMER (18000 MW) 0.9 g/100 g; COCAMIDOPROPYL BETAINE 14 g/100 g; GLYCERIN 3 g/100 g; AMINO ACIDS, SILK 0.011 g/100 g; CETRIMONIUM CHLORIDE 0.075 g/100 g; PROPANEDIOL 0.05 g/100 g; LINALOOL, (+/-)- 0.03 g/100 g; GLYCOL DISTEARATE 2.5 g/100 g; ALOE VERA LEAF 0.001 g/100 g; LAVENDER OIL 0.01 g/100 g; BUTYLPHENYL METHYLPROPIONAL 0.075 g/100 g; COUMARIN 0.04 g/100 g

BioSilk Antibacterial Shampoo

Warnings

For external use only.
When using this product
do not use in or near eyes
if contact occurs, rinse eyes thoroughly
with water
Stop use and ask a doctor if
irritation and redness develop
Keep out of reach of children.
In case of accidental ingestion, get
medical help or contact a Poison
Control Center immediately.

Directions

apply to wet hair and
lather rinse thoroughly
can be used daily

USE

Use as a shampoo to help reduce bacteria

Active ingredient

Active ingredient Purpose
Benzalkonium Chloride 0.10% Antimicrobial

Stop use and ask a doctor if
irritation and redness develop

Keep out of reach of children

In case of accidental ingestion, get
medical help or contact a Poison
Control Center immediately.

When using this product

do not use in or near eyes
if contact occurs, rinse eyes thoroughly
with water

Purpose

Antimicrobial

Inactive Ingredients

Aqua/Water/Eau,
Cocamidopropyl
Betaine,
Cocamidopropyl
Hydroxysultaine,
Glycerin, Glycol
Distearate, Decyl
Glucoside, Aloe
Barbadensis Leaf Juice,
Lavandula Angustifolia
(Lavender) Oil,
Hydrolyzed Silk,
Acrylates Copolymer,
PEG-150 Pentaerythrityl
Tetrastearate, Caprylyl
Glycol,
Polyquaternium-10, PEG-6
Caprylic/Capric Glycerides,
Hexylene Glycol, Disodium
EDTA, Pentylene Glycol,
Ethylhexylglycerin,
Cetrimonium Chloride,
Propanediol, Alcohol Denat.,
Fragrance (Parfum), Benzyl
Benzoate, Butylphenyl
Methylpropional, Coumarin, Linalool

Biosilk H+B Shampoo

Biosilk

Health + Beauty

Antibacterial Shampoo

with aloe vera, lavender & silk

94% natural

Kills 99.9% of germs

FDA Registration #

NDC 73740-7070-1

sulfate and paraben free

pH 5.5

Made in the USA

12 Fl OZ (355 mL)